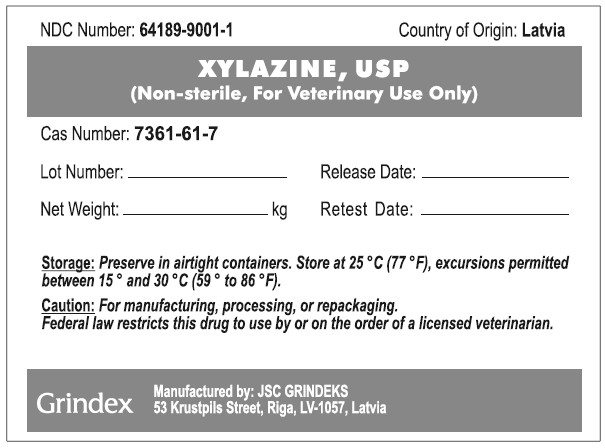 DRUG LABEL: Xylazine
NDC: 64189-9001 | Form: POWDER
Manufacturer: GRINDEKS Joint Stock Company
Category: other | Type: BULK INGREDIENT - ANIMAL DRUG
Date: 20251216

ACTIVE INGREDIENTS: XYLAZINE 1 kg/1 kg

Xylazine, USP

WARNINGS AND PRECAUTIONS

Caution: For manufacturing, processing, or repackaging.

Federal law restricts this drug to use by or on the order of a licensed veterinarian.

STORAGE AND HANDLING

Storage: Preserve in airtight containers. Store at 25°C (77°F), excursions permitted between 15° and 30°C (59° to 86°F).

PACKAGE LABEL

NDC Number: 64189-9001-1 Country of Origin: Latvia

XYLAZINE, USP

(Non-sterile, For Veterinary Use Only)

Cas Number: 7361-61-7

Lot Number:_______________ Release Date:____________

Net Weight:_______________kg Retest Date:_____________

Storage: Preserve in airtight containers. Store at 25°C (77°F), excursions permitted between 15° and 30°C (59° to 86°F).

Caution: For manufacturing, processing, or repackaging. Federal law restricts this drug to use by or on the order of a licensed veterinarian.

Grindex

Manufactured by: JSC GRINDEKS

53 Krustpils Street, Riga, LV-1057, Latvia